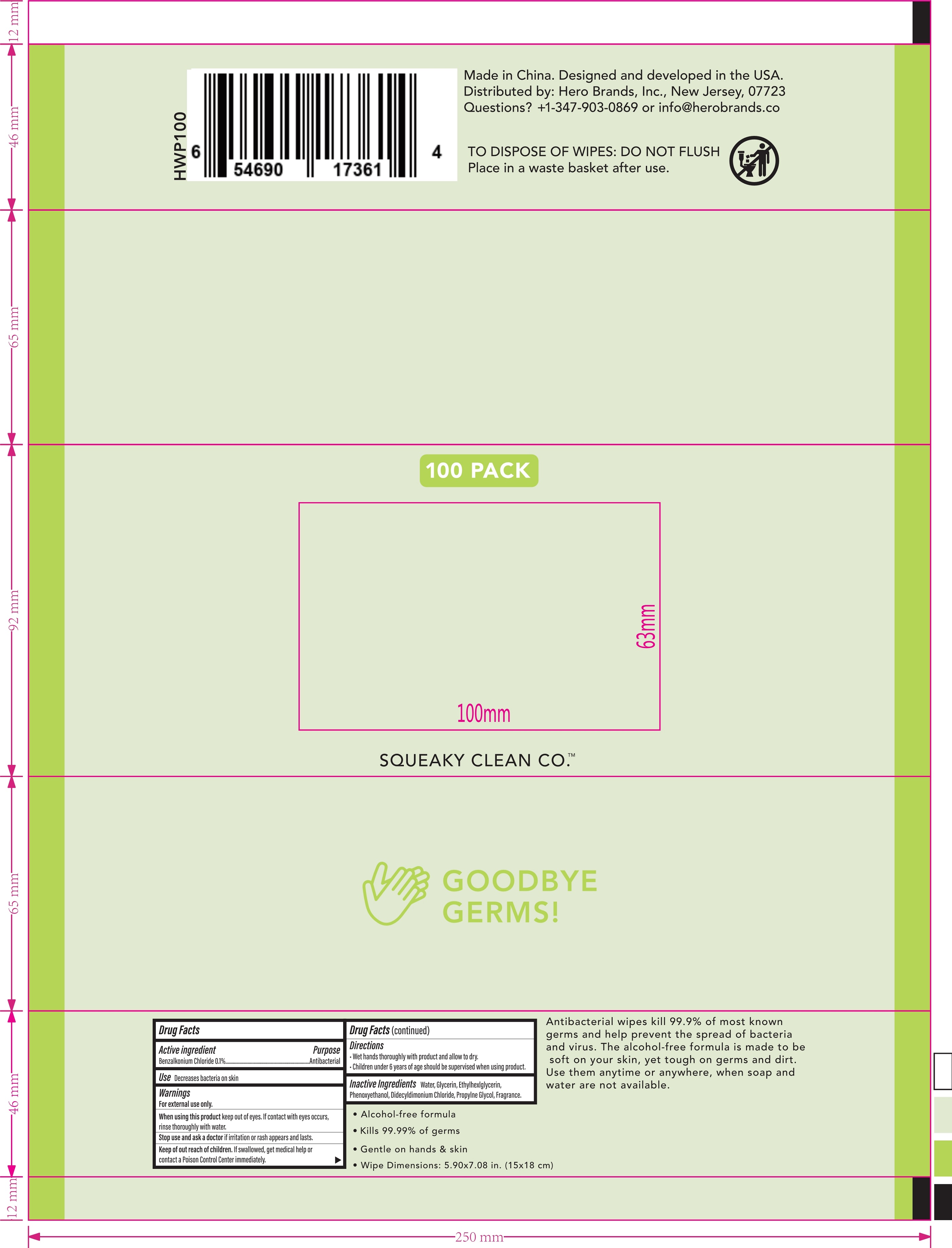 DRUG LABEL: WET WIPES
NDC: 75662-006 | Form: CLOTH
Manufacturer: Ningbo Chenxing Daily Necessities Co., Ltd.
Category: otc | Type: HUMAN OTC DRUG LABEL
Date: 20200910

ACTIVE INGREDIENTS: BENZALKONIUM CHLORIDE 0.1 g/100 g
INACTIVE INGREDIENTS: DIDECYLDIMONIUM CHLORIDE; ETHYLHEXYLGLYCERIN; PROPYLENE GLYCOL; GLYCERIN; PHENOXYETHANOL; WATER

75662-006 WET WIPES

Active Ingredient(s)

Benzalkonium Chloride 0.1%. Purpose: Antiseptic

Purpose

Antiseptic, Wet Wipes

Use

Hand sanitizer to reduce bacteria on the skin

Warnings

For external use only.

Do not use

- if you are allergic to any of the ingredients.
- on children less than 2 years of age unless directed by a doctor.
- as a diaper wipe or for personal cleaning

When using this product do not use in or near the eyes.

In case of eye contact, rinse eyes thoroughly eyes with water.

Stop use and ask a doctor if signs of irritation or rash appears and lasts.

KEEP OUT OF REACH OF CHILDREN

Keep out of the reach of children. If swallowed, get medical help or contact a Poison Control Center right away.

Directions

- Wet hands thoroughly with product and allow to dry.
- Discard wipes in trash receptacle after use. Do not flush.
- Children under 6 years of age should be supervised when using this product.

Inactive ingredients

Purified water, Phenoxyethanol, Ethylhexyl Glycerin, Propylene Glycol, Didecyldimonium Chloride, Glycerin

Package Label - Principal Display Panel

75662-006-01 100 wipes